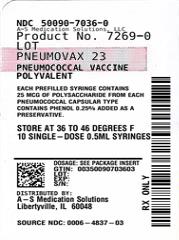 DRUG LABEL: PNEUMOVAX 23
NDC: 50090-7036 | Form: INJECTION, SOLUTION
Manufacturer: A-S Medication Solutions
Category: other | Type: VACCINE LABEL
Date: 20251003

ACTIVE INGREDIENTS: STREPTOCOCCUS PNEUMONIAE TYPE 1 CAPSULAR POLYSACCHARIDE ANTIGEN 25 ug/0.5 mL; STREPTOCOCCUS PNEUMONIAE TYPE 2 CAPSULAR POLYSACCHARIDE ANTIGEN 25 ug/0.5 mL; STREPTOCOCCUS PNEUMONIAE TYPE 3 CAPSULAR POLYSACCHARIDE ANTIGEN 25 ug/0.5 mL; STREPTOCOCCUS PNEUMONIAE TYPE 4 CAPSULAR POLYSACCHARIDE ANTIGEN 25 ug/0.5 mL; STREPTOCOCCUS PNEUMONIAE TYPE 5 CAPSULAR POLYSACCHARIDE ANTIGEN 25 ug/0.5 mL; STREPTOCOCCUS PNEUMONIAE TYPE 6B CAPSULAR POLYSACCHARIDE ANTIGEN 25 ug/0.5 mL; STREPTOCOCCUS PNEUMONIAE TYPE 7F CAPSULAR POLYSACCHARIDE ANTIGEN 25 ug/0.5 mL; STREPTOCOCCUS PNEUMONIAE TYPE 8 CAPSULAR POLYSACCHARIDE ANTIGEN 25 ug/0.5 mL; STREPTOCOCCUS PNEUMONIAE TYPE 9N CAPSULAR POLYSACCHARIDE ANTIGEN 25 ug/0.5 mL; STREPTOCOCCUS PNEUMONIAE TYPE 9V CAPSULAR POLYSACCHARIDE ANTIGEN 25 ug/0.5 mL; STREPTOCOCCUS PNEUMONIAE TYPE 10A CAPSULAR POLYSACCHARIDE ANTIGEN 25 ug/0.5 mL; STREPTOCOCCUS PNEUMONIAE TYPE 11A CAPSULAR POLYSACCHARIDE ANTIGEN 25 ug/0.5 mL; STREPTOCOCCUS PNEUMONIAE TYPE 12F CAPSULAR POLYSACCHARIDE ANTIGEN 25 ug/0.5 mL; STREPTOCOCCUS PNEUMONIAE TYPE 14 CAPSULAR POLYSACCHARIDE ANTIGEN 25 ug/0.5 mL; STREPTOCOCCUS PNEUMONIAE TYPE 15B CAPSULAR POLYSACCHARIDE ANTIGEN 25 ug/0.5 mL; STREPTOCOCCUS PNEUMONIAE TYPE 17F CAPSULAR POLYSACCHARIDE ANTIGEN 25 ug/0.5 mL; STREPTOCOCCUS PNEUMONIAE TYPE 18C CAPSULAR POLYSACCHARIDE ANTIGEN 25 ug/0.5 mL; STREPTOCOCCUS PNEUMONIAE TYPE 19F CAPSULAR POLYSACCHARIDE ANTIGEN 25 ug/0.5 mL; STREPTOCOCCUS PNEUMONIAE TYPE 19A CAPSULAR POLYSACCHARIDE ANTIGEN 25 ug/0.5 mL; STREPTOCOCCUS PNEUMONIAE TYPE 20 CAPSULAR POLYSACCHARIDE ANTIGEN 25 ug/0.5 mL; STREPTOCOCCUS PNEUMONIAE TYPE 22F CAPSULAR POLYSACCHARIDE ANTIGEN 25 ug/0.5 mL; STREPTOCOCCUS PNEUMONIAE TYPE 23F CAPSULAR POLYSACCHARIDE ANTIGEN 25 ug/0.5 mL; STREPTOCOCCUS PNEUMONIAE TYPE 33F CAPSULAR POLYSACCHARIDE ANTIGEN 25 ug/0.5 mL
INACTIVE INGREDIENTS: PHENOL

HIGHLIGHTS OF PRESCRIBING INFORMATION

These highlights do not include all the information needed to use PNEUMOVAX 23 safely and effectively. See full prescribing information for PNEUMOVAX 23.
PNEUMOVAX® 23 (pneumococcal vaccine polyvalent)
Sterile, Liquid Vaccine for Intramuscular or Subcutaneous
Injection
Initial U.S. Approval: 1983

1 INDICATIONS AND USAGE

PNEUMOVAX 23 is a vaccine indicated for active immunization for the prevention of pneumococcal disease caused by the 23 serotypes contained in the vaccine (1, 2, 3, 4, 5, 6B, 7F, 8, 9N, 9V, 10A, 11A, 12F, 14, 15B, 17F, 18C, 19F, 19A, 20, 22F, 23F, and 33F). (1.1)

PNEUMOVAX 23 is approved for use in persons 50 years of age or older and persons aged ≥2 years who are at increased risk for pneumococcal disease. (1.1, 14.1)

2 DOSAGE AND ADMINISTRATION

Single 0.5-mL dose of PNEUMOVAX 23 administered intramuscularly or subcutaneously only. (2.2)

3 DOSAGE FORMS AND STRENGTHS

Clear, sterile solution supplied in a (0.5-mL dose) single-dose vial and a single-dose, prefilled syringe. (3)

4 CONTRAINDICATIONS

Severe allergic reaction (e.g., anaphylaxis) to any component of PNEUMOVAX 23. (4.1)

5 WARNINGS AND PRECAUTIONS

- Use caution and appropriate care for individuals with severely compromised cardiovascular and/or pulmonary function in whom a systemic reaction would pose a significant risk. (5.2)

6 ADVERSE REACTIONS

The most common adverse reactions, reported in >10% of subjects vaccinated with PNEUMOVAX 23 for the first time in a clinical trial, were: injection-site pain/soreness/tenderness (60.0%), injection-site swelling/induration (20.3%), headache (17.6%), injection-site erythema (16.4%), asthenia and fatigue (13.2%), and myalgia (11.9%). (6.1)

To report SUSPECTED ADVERSE REACTIONS, contact Merck Sharp & Dohme LLC at 1-877-888-4231 or VAERS at 1-800-822-7967 or www.vaers.hhs.gov.

7 DRUG INTERACTIONS

In a randomized clinical study, a reduced immune response to ZOSTAVAX® as measured by gpELISA was observed in individuals who received concurrent administration of PNEUMOVAX 23 and ZOSTAVAX compared with individuals who received these vaccines 4 weeks apart. Consider administration of the two vaccines separated by at least 4 weeks. (7.1, 14.3)

8 USE IN SPECIFIC POPULATIONS

Pediatrics: PNEUMOVAX 23 is not approved for use in children younger than 2 years of age because children in this age group do not develop an effective immune response to capsular types contained in the polysaccharide vaccine. (8.4)

Geriatrics: For subjects aged 65 years or older in a clinical study systemic adverse reactions, determined by the investigator to be vaccine-related, were higher following revaccination (33.1%) than following initial vaccination (21.7%). Routine revaccination of immunocompetent persons previously vaccinated with a 23-valent vaccine, is not recommended. (8.5)

Immunocompromised Individuals: Response to vaccination may be diminished. (5.4, 8.6)

FULL PRESCRIBING INFORMATION

1 INDICATIONS AND USAGE

1.1 Indications and Use

PNEUMOVAX® 23 is a vaccine indicated for active immunization for the prevention of pneumococcal disease caused by the 23 serotypes contained in the vaccine (1, 2, 3, 4, 5, 6B, 7F, 8, 9N, 9V, 10A, 11A, 12F, 14, 15B, 17F, 18C, 19F, 19A, 20, 22F, 23F, and 33F). PNEUMOVAX 23 is approved for use in persons 50 years of age or older and persons aged ≥2 years who are at increased risk for pneumococcal disease.

1.2 Limitations of Use

PNEUMOVAX 23 will not prevent disease caused by capsular types of pneumococcus other than those contained in the vaccine.

2 DOSAGE AND ADMINISTRATION

For intramuscular or subcutaneous injection only.

2.1 Preparation

- Parenteral drug products should be inspected visually for particulate matter and discoloration prior to administration. If either of these two conditions exists, the vaccine should not be administered.
- Do not mix PNEUMOVAX 23 with other vaccines in the same syringe or vial.
- Use a separate sterile syringe and needle for each individual patient to prevent transmission of infectious agents from one person to another.
  Single-Dose Vial
  Withdraw 0.5 mL from the vial using a sterile needle and syringe free of preservatives, antiseptics, and detergents.
  Single-Dose, Prefilled Syringe
  The package does not contain a needle. Attach a sterile needle to the prefilled syringe by twisting in a clockwise direction until the needle fits securely on the syringe.

2.2 Administration

Administer PNEUMOVAX 23 intramuscularly or subcutaneously into the deltoid muscle or lateral mid-thigh. Do not inject intravascularly or intradermally.

Single-Dose Vial

Administer a single 0.5-mL dose of PNEUMOVAX 23 using a sterile needle and syringe. Discard vial after use.

Single-Dose, Prefilled Syringe

Administer the entire contents of the single-dose, prefilled syringe per standard protocol using a sterile needle. Discard syringe after use.

2.3 Revaccination

The Advisory Committee on Immunization Practices (ACIP) has recommendations for revaccination against pneumococcal disease for persons at high risk who were previously vaccinated with PNEUMOVAX 23. Routine revaccination of immunocompetent persons previously vaccinated with a 23-valent vaccine, is not recommended.

3 DOSAGE FORMS AND STRENGTHS

PNEUMOVAX 23 is a clear, sterile solution supplied in a (0.5-mL dose) single-dose vial and a single-dose, prefilled syringe. [See Description (11) and How Supplied/Storage and Handling (16).]

4 CONTRAINDICATIONS

4.1 Hypersensitivity

Do not administer PNEUMOVAX 23 to individuals with a history of anaphylactic/anaphylactoid or severe allergic reaction to any component of the vaccine. [See Description (11).]

5 WARNINGS AND PRECAUTIONS

5.1 Persons with Moderate or Severe Acute Illness

Defer vaccination with PNEUMOVAX 23 in persons with moderate or severe acute illness.

5.2 Persons with Severely Compromised Cardiovascular or Pulmonary Function

Caution and appropriate care should be exercised in administering PNEUMOVAX 23 to individuals with severely compromised cardiovascular and/or pulmonary function in whom a systemic reaction would pose a significant risk.

5.3 Use of Antibiotic Prophylaxis

This vaccine does not replace the need for penicillin (or other antibiotic) prophylaxis against pneumococcal infection. In patients who require penicillin (or other antibiotic) prophylaxis against pneumococcal infection, such prophylaxis should not be discontinued after vaccination with PNEUMOVAX 23.

5.4 Persons with Altered Immunocompetence

Persons who are immunocompromised, including persons receiving immunosuppressive therapy, may have a diminished immune response to PNEUMOVAX 23. [See Use in Specific Populations (8.6).]

5.5 Persons with Chronic Cerebrospinal Fluid Leakage

PNEUMOVAX 23 may not be effective in preventing pneumococcal meningitis in patients who have chronic cerebrospinal fluid (CSF) leakage resulting from congenital lesions, skull fractures, or neurosurgical procedures.

6 ADVERSE REACTIONS

The most common adverse reactions, reported in >10% of subjects vaccinated with PNEUMOVAX 23 for the first time in a clinical trial, were: injection-site pain/soreness/tenderness (60.0%), injection-site swelling/induration (20.3%), headache (17.6%), injection-site erythema (16.4%), asthenia/fatigue (13.2%), and myalgia (11.9%). [See Adverse Reactions (6.1).]

6.1 Clinical Trials Experience

Because clinical trials are conducted under widely varying conditions, adverse reaction rates observed in the clinical trials of a vaccine cannot be directly compared to rates in the clinical trials of another vaccine and may not reflect the rates observed in practice.

Primary Vaccination and Revaccination with PNEUMOVAX 23 in Adults 50 Years of Age or Older

In a randomized, double-blind, placebo-controlled crossover clinical trial, subjects were enrolled in four different cohorts defined by age (50-64 years of age and ≥65 years of age) and vaccination status (no pneumococcal vaccination or receipt of a pneumococcal polysaccharide vaccine 3-5 years prior to the study). Subjects in each cohort were randomized to receive intramuscular injections of PNEUMOVAX 23 followed by placebo (saline containing 0.25% phenol), or placebo followed by PNEUMOVAX 23, at 30-day (±7 days) intervals. The safety of an initial vaccination (first dose) was compared to revaccination (second dose) with PNEUMOVAX 23 for 14 days following each vaccination.

All 1008 subjects (average age, 67 years; 49% male and 51% female; 91% Caucasian, 4.7% African-American, 3.5% Hispanic, and 0.8% Other) received placebo injections.

Initial vaccination was evaluated in a total of 444 subjects (average age 65 years; 32% male and 68% female; 93% Caucasian, 3.2% African-American, 3.4% Hispanic, and 1.1% Other).

Revaccination was evaluated in 564 subjects (average age 69 years; 53% male and 47% female; 90% Caucasian, 3.5% Hispanic, 6.0% African-American, and 0.5% Other).

Serious Adverse Experiences

In this study, 10 subjects had serious adverse experiences within 14 days of vaccination: 6 who received PNEUMOVAX 23 and 4 who received placebo. Serious adverse experiences within 14 days after PNEUMOVAX 23 included angina pectoris, heart failure, chest pain, ulcerative colitis, depression, and headache/tremor/stiffness/sweating. Serious adverse experiences within 14 days after placebo included myocardial infarction complicated with heart failure, alcohol intoxication, angina pectoris, and edema/urinary retention/heart failure/diabetes.

Five subjects reported serious adverse experiences that occurred outside the 14-day follow-up window: 3 who received PNEUMOVAX 23 and 2 who received placebo. Serious adverse experiences after PNEUMOVAX 23 included cerebrovascular accident, lumbar radiculopathy, and pancreatitis/myocardial infarction resulting in death. Serious adverse experiences after placebo included heart failure and motor vehicle accident resulting in death.

Solicited and Unsolicited Reactions

Table 1 presents the adverse event rates for all solicited and unsolicited reactions reported in ≥1% in any group in this study, without regard to causality.

The most common local adverse reactions reported at the injection site after initial vaccination with PNEUMOVAX 23 were pain/tenderness/soreness (60.0%), swelling/induration (20.3%), and erythema (16.4%). The most common systemic adverse experiences were headache (17.6%), asthenia/fatigue (13.2%), and myalgia (11.9%).

The most common local adverse reactions reported at the injection site after revaccination with PNEUMOVAX 23 were pain/soreness/tenderness (77.2%), swelling (39.8%), and erythema (34.5%). The most common systemic adverse reactions with revaccination were headache (18.1%), asthenia/fatigue (17.9%), and myalgia (17.3%). All of these adverse reactions were reported at a rate lower than 10% after receiving a placebo injection.

Table 1: Incidence of Injection-Site and Systemic Complaints in Adults ≥50 Years of Age Receiving Their First (Initial) or Second (Revaccination) Dose of PNEUMOVAX 23 (Pneumococcal Polysaccharide Vaccine, 23 Valent) or Placebo Occurring at ≥1% in Any Group
 | PNEUMOVAX 23 Initial Vaccination | PNEUMOVAX 23 Revaccination [Subjects receiving their second dose of pneumococcal polysaccharide vaccine as PNEUMOVAX 23 approximately 3-5 years after their first dose.] | Placebo Injection [Subjects receiving placebo injection from this study combined over periods.]
 | N=444 | N=564 | N=1008
Number Followed for Safety | 438 | 548 | 984 [The number of subjects receiving placebo followed for injection-site complaints. The corresponding number of subjects followed for systemic complaints was 981.]
 | AE Rate | AE Rate | AE Rate
Injection-Site Complaints
Solicited Events
Pain/Soreness/Tenderness | 60.0% | 77.2% | 7.7%
Swelling/Induration | 20.3% | 39.8% | 2.8%
Erythema | 16.4% | 34.5% | 3.3%
Unsolicited Events
Ecchymosis | 0% | 1.1% | 0.3%
Pruritus | 0.2% | 1.6% | 0.0%
Systemic Complaints
Solicited Events
Asthenia/Fatigue | 13.2% | 17.9% | 6.7%
Chills | 2.7% | 7.8% | 1.8%
Myalgia | 11.9% | 17.3% | 3.3%
Headache | 17.6% | 18.1% | 8.9%
Unsolicited Events
Fever [Fever events include subjects who felt feverish in addition to subjects with elevated temperature.] | 1.4% | 2.0% | 0.7%
Diarrhea | 1.1% | 0.7% | 0.5%
Dyspepsia | 1.1% | 1.1% | 0.9%
Nausea | 1.8% | 1.8% | 0.9%
Back Pain | 0.9% | 0.9% | 1.0%
Neck Pain | 0.7% | 1.5% | 0.2%
Upper Respiratory Infection | 1.8% | 2.6% | 1.8%
Pharyngitis | 1.1% | 0.4% | 1.3%

In this clinical study an increased rate of local reactions was observed with revaccination at 3-5 years following initial vaccination.

For subjects aged 65 years or older, injection-site adverse reaction rate was higher following revaccination (79.3%) than following initial vaccination (52.9%). The proportion of subjects reporting injection site discomfort that interfered with or prevented usual activity or injection site induration ≥4 inches was higher following revaccination (30.6%) than following initial vaccination (10.4%). Injection site reactions typically resolved by 5 days following vaccination.

For subjects aged 50-64 years, the injection-site adverse reaction rate for revaccinees and initial vaccinees was similar (79.6% and 72.8% respectively).

The rate of systemic adverse reactions was similar among both initial vaccinees and revaccinees within each age group. The rate of vaccine-related systemic adverse reactions was higher following revaccination (33.1%) than following initial vaccination (21.7%) in subjects 65 years of age or older, and was similar following revaccination (37.5%) and initial vaccination (35.5%) in subjects 50-64 years of age. The most common systemic adverse reactions reported after PNEUMOVAX 23 were as follows: asthenia/fatigue, myalgia and headache.

Regardless of age, the observed increase in post vaccination use of analgesics (≤13% in the revaccinees and ≤4% in the initial vaccinees) returned to baseline by day 5.

Sequential Administration of Prevnar 13 and PNEUMOVAX 23

In a randomized, double-blind, placebo-controlled, multicenter study, healthy adults, 50 years of age and older, received Prevnar 13 followed by PNEUMOVAX 23 either 8 weeks later (Group 1) or 26 weeks later (Group 2). Placebo was administered instead of PNEUMOVAX 23 at 26 weeks (Group 1) or 8 weeks (Group 2). Solicited injection site adverse reactions were evaluated during Days 1 through 5 postvaccination. Solicited systemic adverse reactions and any other adverse reactions were evaluated during Days 1 through 14 postvaccination, and any serious adverse events (SAEs) were collected throughout the study period (through Week 30). [See Clinical Studies (14.2).]

Overall, subjects were a mean age of 64.2 years (range: 50 to 97 years). There were more females (n=219, 54.8%) than males (n=181, 45.3%). By race, 84.8% of subjects were White, 9.3% were Black or African-American, and 6.1% were other racial groups; the majority of subjects were not Hispanic or Latino (n=322, 80.5%).

Serious Adverse Reactions

There were 24 SAEs reported in 20 subjects (n=9 [4.5%] Group 1; n=11 [5.5%] Group 2). No SAEs were considered related to vaccination.

Solicited Adverse Reactions

Solicited injection site adverse reactions that occurred during Days 1 through 5 postvaccination with PNEUMOVAX 23, solicited systemic adverse reactions that occurred during Days 1 through 14, and fever that occurred during Days 1 through 5 postvaccination with PNEUMOVAX 23 are presented in Table 2. In this study, 81.4% of subjects in Group 1 and 64.0% of subjects in Group 2 reported at least 1 injection site adverse reaction from Days 1 through 5 postvaccination with PNEUMOVAX 23, and 64.9% of subjects in Group 1 and 54.9% of subjects in Group 2 reported at least 1 systemic adverse reaction from Days 1 through 14 postvaccination with PNEUMOVAX 23.

Table 2: Rates (%) of Solicited Injection Site Reactions Occurring on Days 1 to 5 After PNEUMOVAX 23 and Solicited Systemic Adverse Reactions Occurring on Days 1 to 14 After PNEUMOVAX 23
 | Group 1 [Group 1: 8-week interval between Prevnar 13 and PNEUMOVAX 23.] (Prevnar 13 -> PNEUMOVAX 23 -> Placebo) |  | Group 2 [Group 2: 26-week interval between Prevnar 13 and PNEUMOVAX 23.] (Prevnar 13 -> Placebo -> PNEUMOVAX 23)
 | n | (%) | n | (%)
Injection Site Adverse Reactions
Subjects in population with follow-up | 188 |  | 164
Any injection site reaction | 153 | (81.4) | 105 | (64.0)
Any Injection site pain [Pain was characterized as mild, moderate or severe. (Mild: awareness of sign or symptom, but easily tolerated. Moderate: discomfort enough to cause interference with usual activity. Severe: incapacitating with inability to work or do usual activity).] | 149 | (79.3) | 105 | (64.0)
Mild | 72 | (38.3) | 65 | (39.6)
Moderate | 65 | (34.6) | 36 | (22.0)
Severe [One Group 1 subject with severe pain and swelling greater than 10.2 cm after receipt of PNEUMOVAX 23, went to the Emergency Room for medical attention.] | 12 | (6.4) | 4 | (2.4)
Any Injection site swelling | 95 | (50.5) | 48 | (29.3)
0 to <2.5 cm | 28 | (14.9) | 19 | (11.6)
≥2.5 to <5.1 cm | 20 | (10.6) | 9 | (5.5)
≥5.1 to <7.6 cm | 20 | (10.6) | 10 | (6.1)
≥7.6 to <10.2 cm | 15 | (8.0) | 2 | (1.2)
≥10.2 cm | 12 | (6.4) | 8 | (4.9)
Any Injection site erythema | 78 | (41.5) | 48 | (29.3)
0 to <2.5 cm | 26 | (13.8) | 20 | (12.2)
≥2.5 to <5.1 cm | 12 | (6.4) | 13 | (7.9)
≥5.1 to <7.6 cm | 12 | (6.4) | 6 | (3.7)
≥7.6 to <10.2 cm | 7 | (3.7) | 3 | (1.8)
≥10.2 cm | 19 | (10.1) | 6 | (3.7)
Unknown [missing data] | 2 | (1.1) | 0 | (0.0)
Systemic Adverse Reactions
Subjects in population with follow-up | 188 |  | 164
Any systemic adverse reaction | 122 | (64.9) | 90 | (54.9)
Myalgia | 93 | (49.5) | 70 | (42.7)
Fatigue | 59 | (31.4) | 45 | (27.4)
Headache | 46 | (24.5) | 30 | (18.3)
Arthralgia | 37 | (19.7) | 25 | (15.2)
Subjects with temperature data [Percentages are calculated based on number of subjects with temperature data. Oral temperature was solicited on Days 1 to 5 after PNEUMOVAX 23 vaccination.] | 185 |  | 161
Temperature ≥ 100.4°F | 1 | (0.5) | 0 | (0.0)
Every subject is counted a single time for each applicable row and column.
A specific adverse reaction appears in this table only if its incidence in one or more of the columns meets the incidence criterion in the table title, after rounding.

6.2 Post-Marketing Experience

The following list of adverse reactions includes those identified during post approval use of PNEUMOVAX 23. Because these reactions are reported voluntarily from a population of uncertain size, it is not always possible to reliably estimate their frequency or their causal relationship to product exposure.

General disorders and administration site conditions
Cellulitis
Malaise
Fever (>102°F)
Warmth at the injection site
Decreased limb mobility
Peripheral edema in the injected extremity
Injection-site necrosis

Digestive System
Nausea
Vomiting

Hematologic/Lymphatic
Lymphadenitis
Lymphadenopathy
Thrombocytopenia in patients with stabilized idiopathic thrombocytopenic purpura
Hemolytic anemia in patients who have had other hematologic disorders
Leukocytosis

Hypersensitivity reactions including
Anaphylactoid reactions
Serum Sickness
Angioneurotic edema

Musculoskeletal System
Arthralgia
Arthritis

Nervous System
Paresthesia
Radiculoneuropathy
Guillain-Barré syndrome
Febrile convulsion

Skin
Rash
Urticaria
Cellulitis-like reactions
Erythema multiforme

Investigations
Increased serum C-reactive protein

7 DRUG INTERACTIONS

7.1 Concomitant Administration with Other Vaccines

In a randomized clinical study, a reduced immune response to ZOSTAVAX® as measured by gpELISA was observed in individuals who received concurrent administration of PNEUMOVAX 23 and ZOSTAVAX compared with individuals who received these vaccines 4 weeks apart. Consider administration of the two vaccines separated by at least 4 weeks. [See Clinical Studies (14.3).]

Limited safety and immunogenicity data from clinical trials are available on the concurrent administration of PNEUMOVAX 23 and vaccines other than ZOSTAVAX.

8 USE IN SPECIFIC POPULATIONS

8.1 Pregnancy

Risk Summary

All pregnancies have a background risk of birth defect, loss, or other adverse outcomes. In the U.S. general population, the estimated background risk of major birth defects and miscarriage in clinically recognized pregnancies is 2-4% and 15-20%, respectively.

Available human data from clinical trials of PNEUMOVAX 23 in pregnancy have not established the presence or absence of a vaccine-associated risk.

Developmental toxicity studies have not been conducted with PNEUMOVAX 23 in animals.

8.2 Lactation

Risk Summary

It is not known whether PNEUMOVAX 23 is excreted in human milk. Data are not available to assess the effects of PNEUMOVAX 23 on the breastfed infant or on milk production/excretion.

The developmental and health benefits of breastfeeding should be considered along with the mother's clinical need for PNEUMOVAX 23 and any potential adverse effects on the breastfed child from PNEUMOVAX 23 or from the underlying maternal condition. For preventive vaccines, the underlying maternal condition is susceptibility to the disease prevented by the vaccine.

8.4 Pediatric Use

PNEUMOVAX 23 is not approved for use in children less than 2 years of age. Children in this age group do not develop an effective immune response to the capsular types contained in this polysaccharide vaccine.

The ACIP has recommendations for use of PNEUMOVAX 23 in children 2 years of age or older, who have previously received pneumococcal vaccines, and who are at increased risk for pneumococcal disease.

8.5 Geriatric Use

In one clinical trial of PNEUMOVAX 23, conducted post-licensure, a total of 629 subjects who were aged ≥65 years and 201 subjects who were aged ≥75 years were enrolled.

In this trial, the safety of PNEUMOVAX 23 in adults 65 years of age and older (N=629) was compared to the safety of PNEUMOVAX 23 in adults 50 to 64 years of age (N=379). The subjects in this study had underlying chronic illness but were in stable condition; at least 1 medical condition at enrollment was reported by 86.3% of subjects who were 50 to 64 years old, and by 96.7% of subjects who were 65 to 91 years old. The rate of vaccine-related systemic adverse experiences was higher following revaccination (33.1%) than following primary vaccination (21.7%) in subjects ≥65 years of age, and was similar following revaccination (37.5%) and primary vaccination (35.5%) in subjects 50 to 64 years of age.

Since elderly individuals may not tolerate medical interventions as well as younger individuals, a higher frequency and/or a greater severity of reactions in some older individuals cannot be ruled out.

Post-marketing reports have been received in which some elderly individuals had severe adverse experiences and a complicated clinical course following vaccination. Some individuals with underlying medical conditions of varying severity experienced local reactions and fever associated with clinical deterioration requiring hospital care.

8.6 Immunocompromised Individuals

Persons who are immunocompromised, including persons receiving immunosuppressive therapy, may have a diminished immune response to PNEUMOVAX 23.

11 DESCRIPTION

PNEUMOVAX 23 (Pneumococcal Vaccine Polyvalent) is a sterile, liquid vaccine consisting of a mixture of purified capsular polysaccharides from Streptococcus pneumoniae types (1, 2, 3, 4, 5, 6B, 7F, 8, 9N, 9V, 10A, 11A, 12F, 14, 15B, 17F, 18C, 19F, 19A, 20, 22F, 23F, and 33F).

PNEUMOVAX 23 is a clear, colorless solution. Each 0.5-mL dose of vaccine contains 25 micrograms of each polysaccharide type in isotonic saline solution containing 0.25% phenol as a preservative. The vaccine is used directly as supplied. No dilution or reconstitution is necessary.

The vial stoppers, syringe plunger stopper and syringe tip cap are not made with natural rubber latex.

12 CLINICAL PHARMACOLOGY

12.1 Mechanism of Action

PNEUMOVAX 23 induces type-specific antibodies that enhance opsonization, phagocytosis, and killing of pneumococci by leukocytes and other phagocytic cells. The levels of antibodies that correlate with protection against pneumococcal disease have not been clearly defined.

14 CLINICAL STUDIES

14.1 Effectiveness

The protective efficacy of pneumococcal vaccines containing six (types 1, 2, 4, 8, 12F, and 25) or twelve (types 1, 2, 3, 4, 6A, 8, 9N, 12F, 25, 7F, 18C, and 46) capsular polysaccharides was investigated in two controlled studies in South Africa in male novice gold miners ranging in age from 16 to 58 years, in whom there was a high attack rate for pneumococcal pneumonia and bacteremia. In both studies, participants in the control groups received either meningococcal polysaccharide serogroup A vaccine or saline placebo. In both studies, attack rates for vaccine type pneumococcal pneumonia were observed for the period from 2 weeks through about 1 year after vaccination. Protective efficacy was 76% and 92%, respectively, for the 6- and 12-valent vaccines, for the capsular types represented.

Three similar studies in South African young adult male novice gold miners were carried out by Dr. R. Austrian and associates using similar pneumococcal vaccines prepared for the National Institute of Allergy and Infectious Diseases, with pneumococcal vaccines containing a 6-valent formulation (types 1, 3, 4, 7, 8, and 12) or a 13-valent formulation (types 1, 2, 3, 4, 6, 7, 8, 9, 12, 14, 18, 19, and 25) capsular polysaccharides. The reduction in pneumococcal pneumonia caused by the capsular types contained in the vaccines was 79%. Reduction in type-specific pneumococcal bacteremia was 82%.

A prospective study in France found a pneumococcal vaccine containing fourteen (types 1, 2, 3, 4, 6A, 7F, 8, 9N, 12F, 14, 18C, 19F, 23F, and 25) capsular polysaccharides to be 77% (95%CI: 51% to 89%) effective in reducing the incidence of pneumonia among male and female nursing home residents with a mean age of 74 (standard deviation of 4 years).

In a study using a pneumococcal vaccine containing eight (types 1, 3, 6, 7, 14, 18, 19, and 23) capsular polysaccharides, vaccinated children and young adults aged 2 to 25 years who had sickle cell disease, congenital asplenia, or undergone a splenectomy experienced significantly less bacteremic pneumococcal disease than patients who were not vaccinated.

In the United States, one post-licensure randomized controlled trial, in the elderly or patients with chronic medical conditions who received a 14-valent pneumococcal polysaccharide vaccine (types 1, 2, 3, 4, 6A, 8, 9N, 12F, 14, 19F, 23F, 25, 7F, and 18C), did not support the efficacy of the vaccine for nonbacteremic pneumonia.

A retrospective cohort analysis study based on the U.S. Centers for Disease Control and Prevention (CDC) pneumococcal surveillance system, showed 57% (95%CI: 45% to 66%) overall protective effectiveness against invasive infections caused by serotypes included in PNEUMOVAX 23 in persons ≥6 years of age, 65 to 84% effectiveness among specific patient groups (e.g., persons with diabetes mellitus, coronary vascular disease, congestive heart failure, chronic pulmonary disease, and anatomic asplenia) and 75% (95%CI: 57% to 85%) effectiveness in immunocompetent persons aged ≥65 years of age. Vaccine effectiveness could not be confirmed for certain groups of immunocompromised patients.

14.2 Immunogenicity

The levels of antibodies that correlate with protection against pneumococcal disease have not been clearly defined.

Antibody responses to most pneumococcal capsular types are generally low or inconsistent in children less than 2 years of age.

Sequential Administration of Prevnar 13 and PNEUMOVAX 23

In a randomized, double-blind, placebo-controlled, multicenter study, healthy adults, 50 years of age and older, received Prevnar 13 followed by PNEUMOVAX 23 either 8 weeks later (Group 1) or 26 weeks later (Group 2). Four hundred subjects were randomized 1:1 into Group 1 or Group 2, all of whom were initially vaccinated with Prevnar 13; of these, 188 subjects received PNEUMOVAX 23 (Group 1) and 185 subjects received placebo (Group 2) at Week 8, and 172 subjects received placebo (Group 1) and 164 subjects received PNEUMOVAX 23 (Group 2) at Week 26.

Opsonophagocytic activity (OPA) titers were measured at prevaccination, at Week 12 and at Week 30 for the 12 shared serotypes contained in both PNEUMOVAX 23 and Prevnar 13 (1, 3, 4, 5, 6B, 7F, 9V, 14, 18C, 19A, 19F, and 23F), 2 of the 11 serotypes unique to PNEUMOVAX 23 (22F and 33F), and 1 serotype unique to Prevnar 13 (6A). OPA testing was performed on evaluable serum samples from all subjects at baseline (Day 1) and Week 12, and on sera from a random subset of subjects (approximately 50% of subjects) at Week 30. Estimated GMTs, GMT ratio, and 95% confidence intervals were obtained from a constrained Longitudinal Data Analysis model {1}.

For each of the shared serotypes, Week 12 OPA geometric mean titers (GMTs) in Group 1 were noninferior to those of Group 2, as the lower bounds of the 95% CIs for the OPA GMT ratios were >0.5 for all 12 shared serotypes. For serotypes 22F and 33F, OPA GMTs in Group 1 at Week 12 were superior to those of Group 2 at Week 12, as the lower bounds of the 95% CIs for the OPA GMT ratios were >2.0 for both serotypes.

The OPA GMTs to the 12 shared serotypes and 2 unique serotypes (22F and 33F) when measured 4 weeks after dosing with PNEUMOVAX 23 were generally similar between Group 1 (Week 12) and Group 2 (Week 30 subset).

14.3 Concomitant Administration with Other Vaccines

In a double-blind, controlled clinical trial, 473 adults, 60 years of age or older, were randomized to receive ZOSTAVAX and PNEUMOVAX 23 concomitantly (N=237), or PNEUMOVAX 23 alone followed 4 weeks later by ZOSTAVAX alone (N=236). At four weeks postvaccination, the varicella-zoster virus (VZV) antibody levels following concomitant use were significantly lower than the VZV antibody levels following nonconcomitant administration (GMTs of 338 vs. 484 gpELISA units/mL, respectively; GMT ratio = 0.70 (95% CI: [0.61, 0.80]).

Limited safety and immunogenicity data from clinical trials are available on the concurrent administration of PNEUMOVAX 23 and vaccines other than ZOSTAVAX.

15 REFERENCES

1. Liang KY, Zeger S. Longitudinal data analysis of continuous and discrete responses for pre-post designs. Sankhyā: The Indian Journal of Statistics (Series B) 2000; 62: 134-148.

16 HOW SUPPLIED/STORAGE AND HANDLING

Product: 50090-7036

17 PATIENT COUNSELING INFORMATION

Advise the patient to read the FDA-approved patient labeling (Patient Information).

- Inform the patient, parent or guardian of the benefits and risks associated with vaccination.
- Tell the patient, parent or guardian that vaccination with PNEUMOVAX 23 may not offer 100% protection from pneumococcal infection.
- Provide the patient, parent or guardian with the vaccine information statements required by the National Childhood Vaccine Injury Act of 1986, with each immunization.
- Instruct the patient, parent or guardian to report any serious adverse reactions to their health care provider who in turn should report such events to the vaccine manufacturer or the U.S. Department of Health and Human Services through the Vaccine Adverse Event Reporting System (VAERS), 1-800-822-7967, or report online at www.vaers.hhs.gov.

Manuf. and Dist. by: Merck Sharp & Dohme LLC
Rahway, NJ 07065, USA

For patent information: www.msd.com/research/patent

The trademarks depicted herein are owned by their respective companies.

Copyright © 1986-2023 Merck & Co., Inc., Rahway, NJ, USA, and its affiliates.
All rights reserved.

uspi-v110-i-2304r045

Patient Information about
PNEUMOVAX® 23 (pronounced "noo-mo-vax 23")
Generic Name: pneumococcal vaccine polyvalent

Read this leaflet before you or your child gets the vaccine called PNEUMOVAX 23. If you have any questions about the vaccine after you read this, you should ask your health care provider. This is a summary only. It does not take the place of talking to your doctor, nurse or other health care provider about the vaccine. Only your health care provider can decide if PNEUMOVAX 23 is right for you or your child.

What is PNEUMOVAX 23?

PNEUMOVAX 23 is a vaccine that is given as a shot. It helps protect you from infection by certain germs or bacteria which are called pneumococcus (pronounced "noo-mo-ca-cus"). PNEUMOVAX 23 is for people 50 years of age and older. It is also for people who are 2 years of age and older if they have certain medical conditions that put them at increased risk for infection.

Illnesses or health problems may allow these germs to spread into the blood, lungs, or brain where they can cause serious diseases such as:

- An infection in the blood
- A lung infection (pneumonia) that can also come with an infection in the blood
- An infection of the coverings of the brain and spinal cord (meningitis).

PNEUMOVAX 23 may not protect everyone who gets it. It will not protect against diseases that are caused by bacteria types that are not in the vaccine.

Who should not get PNEUMOVAX 23?

You should not get this vaccine if you (or your child):

- are allergic to any of its ingredients
- had an allergic reaction to PNEUMOVAX 23 in the past
- are less than 2 years old.

What should I tell my health care provider before getting PNEUMOVAX 23?

Tell your health care provider if you (or your child):

- are allergic to PNEUMOVAX 23
- have heart or lung problems
- have a fever
- have immune problems or are receiving radiation treatment for chemotherapy
- are pregnant or breast-feeding

How is PNEUMOVAX 23 given?

Most often, just one shot is given.

If you or your child is in a high-risk group for pneumococcal infection, then your health care provider will decide if it would be helpful to give a second shot of PNEUMOVAX 23 at a later time.

Can PNEUMOVAX 23 be given with other vaccines?

Talk to your health care provider if you plan to get ZOSTAVAX at the same time as PNEUMOVAX 23 because it may be better to get these vaccines at least 4 weeks apart.

Talk to your health care provider if you plan to get PNEUMOVAX 23 at the same time as other vaccines.

What are the possible side effects of PNEUMOVAX 23?

The most common side effects are:

- pain, warmth, soreness, redness, swelling, and hardening at the injection site
- headache
- weakness, feeling tired
- muscle pain

Tell your health care provider or get emergency help right away if you get any of the following problems after vaccination because these may be signs of an allergic reaction or other serious conditions:

- difficulty breathing
- wheezing
- rash
- hives

Side effects at the site where you get the shot may be more common and may feel worse after a second shot than after the first shot.

Tell your health care provider if you or your child has a side effect that bothers you or that does not go away.

For a more complete list of side effects, ask your health care provider.

You may also report any side effect to your or your child's health care provider, or directly to the Vaccine Adverse Event Reporting System (VAERS). You may call the VAERS number 1-800-822-7967 at no charge, or report online to www.vaers.hhs.gov.

What are the ingredients of PNEUMOVAX 23?

Active Ingredients: | Bacterial sugars from 23 pneumococcal types: 1, 2, 3, 4, 5, 6B, 7F, 8, 9N, 9V, 10A, 11A, 12F, 14, 15B, 17F, 18C, 19F, 19A, 20, 22F, 23F, and 33F
Inactive Ingredients: | Phenol (a preservative)

What else should I know about PNEUMOVAX 23?

Some adults and children have problems with leakage of spinal fluid after the skull is cracked or injured or after medical operations and this may increase their risk for pneumococcal infection. PNEUMOVAX 23 may not be able to prevent all of these infections.

The vial stoppers, syringe plunger stopper and syringe tip cap for PNEUMOVAX 23 are not made with natural rubber latex.

This leaflet is a summary of information about PNEUMOVAX 23. If you would like more information, talk to your health care provider or call 1-800-622-4477.

Manuf. and Dist. by: Merck Sharp & Dohme LLC
Rahway, NJ 07065, USA

For patent information: www.msd.com/research/patent

Copyright © 2011-2023 Merck & Co., Inc., Rahway, NJ, USA, and its affiliates.
All rights reserved.

Revised: 04/2023

usppi-v110-i-2304r041